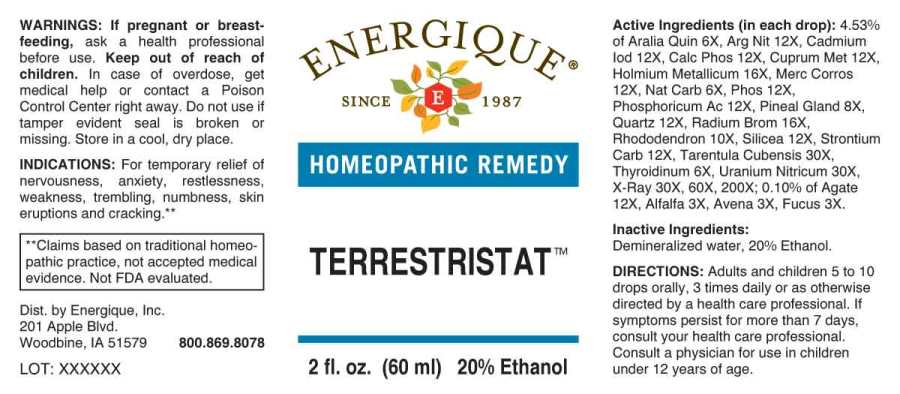 DRUG LABEL: Terrestristat
NDC: 44911-0534 | Form: LIQUID
Manufacturer: Energique, Inc.
Category: homeopathic | Type: HUMAN OTC DRUG LABEL
Date: 20240703

ACTIVE INGREDIENTS: ALFALFA 3 [hp_X]/1 mL; AVENA SATIVA FLOWERING TOP 3 [hp_X]/1 mL; FUCUS VESICULOSUS 3 [hp_X]/1 mL; AMERICAN GINSENG 6 [hp_X]/1 mL; SODIUM CARBONATE 6 [hp_X]/1 mL; THYROID 6 [hp_X]/1 mL; SUS SCROFA PINEAL GLAND 8 [hp_X]/1 mL; RHODODENDRON AUREUM LEAF 10 [hp_X]/1 mL; SILICON DIOXIDE 12 [hp_X]/1 mL; SILVER NITRATE 12 [hp_X]/1 mL; CADMIUM IODIDE 12 [hp_X]/1 mL; TRIBASIC CALCIUM PHOSPHATE 12 [hp_X]/1 mL; COPPER 12 [hp_X]/1 mL; MERCURIC CHLORIDE 12 [hp_X]/1 mL; PHOSPHORIC ACID 12 [hp_X]/1 mL; PHOSPHORUS 12 [hp_X]/1 mL; STRONTIUM CARBONATE 12 [hp_X]/1 mL; HOLMIUM 16 [hp_X]/1 mL; RADIUM BROMIDE 16 [hp_X]/1 mL; CITHARACANTHUS SPINICRUS 30 [hp_X]/1 mL; URANYL NITRATE HEXAHYDRATE 30 [hp_X]/1 mL; ALCOHOL, X-RAY EXPOSED (1000 RAD) 30 [hp_X]/1 mL
INACTIVE INGREDIENTS: WATER; ALCOHOL

DRUG FACTS:

ACTIVE INGREDIENTS:

(in each drop): 4.53% of Aralia Quinquefolia 6X, Argentum Nitricum 12X, Cadmium Iodatum 12X, Calcarea Phosphorica 12X, Cuprum Metallicum 12X, Holmium Metallicum 16X, Mercurius Corrosivus 12X, Natrum Carbonicum 6X, Phosphoricum Acidum 12X, Phosphorus 12X, Pineal Gland (Suis) 8X, Quartz 12X, Radium Bromatum 16X, Rhododendron Chrysanthum 10X, Silicea 12X, Strontium Carbonicum 12X, Tarentula Cubensis 30X, Thyroidinum (Suis) 6X, Uranium Nitricum 30X, X-Ray 30X, 60X, 200X; 0.10% of Agate 12X, Alfalfa 3X, Avena Sativa 3X, Fucus Vesiculosus 3X.

INDICATIONS:

For temporary relief of nervousness, anxiety, restlessness, weakness, trembling, numbness, skin eruptions and cracking.**

**Claims based on traditional homeopathic practice, not accepted medical evidence. Not FDA evaluated.

WARNINGS:

If pregnant or breast-feeding, ask a health professional before use.

Keep out of reach of children. In case of overdose, get medical help or contact a Poison Control Center right away.

Do not use if tamper evident seal is broken or missing.

Store in a cool, dry place.

Keep out of reach of children. In case of overdose, get medical help or contact a Poison Control Center right away.

DIRECTIONS:

Adults and children 5 to 10 drops orally, 3 times daily or as otherwise directed by a health care professional. If symptoms persist for more than 7 days, consult your health care professional. Consult a physician for use in children under 12 years of age.

INDICATIONS:

For temporary relief of nervousness, anxiety, restlessness, weakness, trembling, numbness, skin eruptions and cracking.**

**Claims based on traditional homeopathic practice, not accepted medical evidence. Not FDA evaluated.

INACTIVE INGREDIENTS:

Demineralized water, 20% Ethanol.

QUESTIONS:

Dist. by Energique, Inc.

201 Apple Blvd.

Woodbine, IA 51579 800.869.8078

PACKAGE DISPLAY LABEL:

ENERGIQUE

SINCE 1987

HOMEOPATHIC REMEDY

TERRESTRISTAT

2 fl. oz. (60 ml)